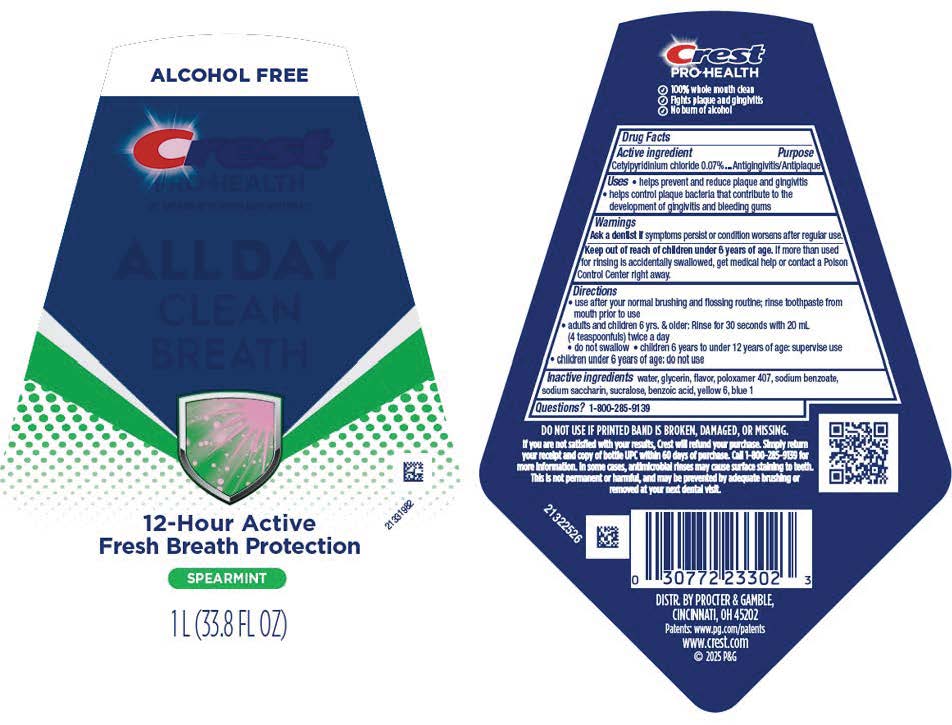 DRUG LABEL: Crest Pro-Health
NDC: 84126-625 | Form: RINSE
Manufacturer: The Procter & Gamble Manufacturing Company
Category: otc | Type: HUMAN OTC DRUG LABEL
Date: 20260121

ACTIVE INGREDIENTS: CETYLPYRIDINIUM CHLORIDE 0.07 g/1 mL
INACTIVE INGREDIENTS: WATER; GLYCERIN; FD&C YELLOW NO. 6; POLOXAMER 407; SODIUM SACCHARIN; SODIUM BENZOATE; FD&C BLUE NO. 1; SUCRALOSE; BENZOIC ACID

Crest PRO-HEALTH ALL DAY CLEAN BREATH

Drug Facts

Active ingredient

Cetylpyridinium chloride 0.07%

Purpose

Antigingivitis/antiplaque

Uses

- helps prevent and reduce plaque and gingivitis
- helps control plaque bacteria that contribute to the development of gingivitis and bleeding gums

Warnings

ASK DOCTOR

Ask a dentist ifsymptoms persist or condition worsens after regular use.

Keep out of reach of children under 6 years of age.If more than used for rinsing is accidentally swallowed, get medical help or contact a Poison Control Center right away.

Directions

- use after your normal brushing and flossing routine; rinse toothpaste from mouth prior to use
- adults and children 6 yrs. & older: Rinse for 30 seconds with 20 mL (4 teaspoonfuls) twice a day
  - do not swallow
  - children 6 years to under 12 years of age: supervise use
- children under 6 years of age: do not use

Inactive ingredients

water, glycerin, flavor, poloxamer 407, sodium benzoate,
sodium saccharin, sucralose, benzoic acid, yellow 6, blue 1

Questions?

1–800–285–9139

DISTR. BY PROCTER & GAMBLE,
CINCINNATI, OH 45202

PRINCIPAL DISPLAY PANEL - 1 L Bottle Label

ALCOHOL FREE

Crest

PRO-HEALTH

CPC ANTIGINGIVITIS/ANTIPLAQUE MOUTHWASH

ALL DAY

CLEAN

BREATH

12-Hour Active

Fresh Breath Protection

SPEARMINT

1 L (33.8FL OZ)